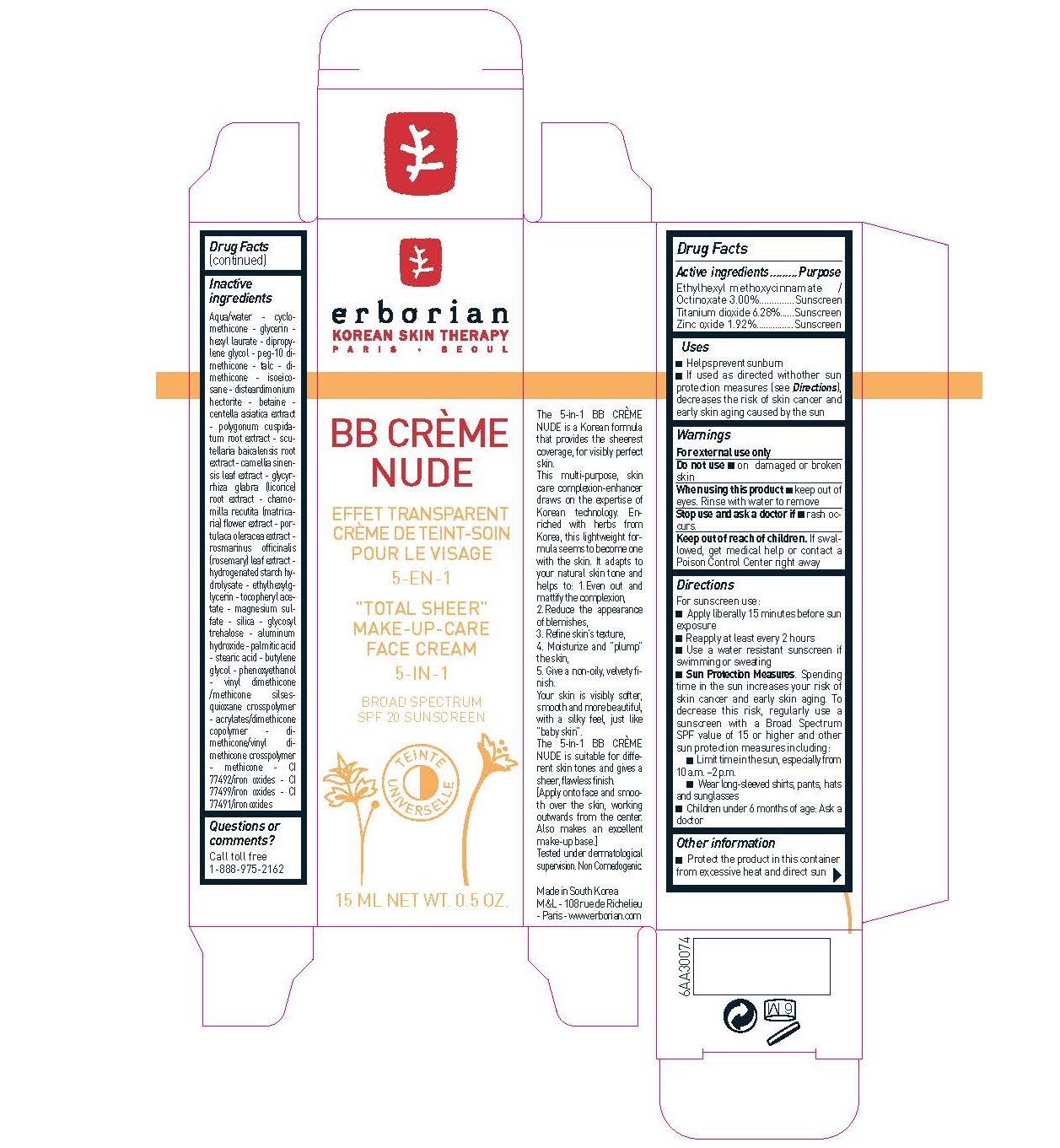 DRUG LABEL: ERBORIAN - BB CREME NUDE SPF20
NDC: 10345-902 | Form: CREAM
Manufacturer: LABORATOIRES M&L
Category: otc | Type: HUMAN OTC DRUG LABEL
Date: 20231215

ACTIVE INGREDIENTS: OCTINOXATE 30 mg/1 mL; TITANIUM DIOXIDE 62.8 mg/1 mL; ZINC OXIDE 19.2 mg/1 mL
INACTIVE INGREDIENTS: WATER; CYCLOMETHICONE; DIPROPYLENE GLYCOL; TALC; DIMETHICONE; ISOEICOSANE; DISTEARDIMONIUM HECTORITE; BETAINE; GLYCYRRHIZA GLABRA; HYDROGENATED STARCH HYDROLYSATE; ETHYLHEXYLGLYCERIN; MAGNESIUM SULFATE, UNSPECIFIED FORM; ALUMINUM HYDROXIDE; PALMITIC ACID; STEARIC ACID; BUTYLENE GLYCOL; PHENOXYETHANOL

ERBORIAN - BB CREME NUDE SPF20

Active ingredients

Octinoxate 3.00% Titanium dioxide 6.28% Zinc oxide 1.92%

Purpose

sunscreen

Uses

-Helps prevent sunburn -If used as directed with other sun protection measures (see Directions), decreases the risk of skin cancer and early skin aging caused by the sun

Warnings

-For external use only. Do not use on damaged or broken skin

-When using this product keep out of eyes. Rinse with water to remove

-Stop use and ask a doctor if rash occurs.

Keep out of reach of children

If swallowed, get medical help or contact a Poison Control Center right away

Directions

For sunscreen use: -Apply liberally 15 minutes before sun exposure -Reapply at least every 2 hours -Use a water resistant sunscreen if swimming or sweating - . Spending time in the sun increases your risk of skin cancer and early skin aging. To decrease this risk, regularly use a sunscreen with a Broad Spectrum SPF value of 15 or higher and other sun protection measures including: -Limit time in the sun, especially from 10 a.m. –2 p.m. -Wear long-sleeved shirts, pants, hats and sunglasses -Children under 6 months of age: Ask a doctor
Sun Protection Measures

Inactive Ingredients

Aqua/water - cyclomethicone- glycerin hexyl laurate - dipropylene glycol - peg-10 dimethicone- talc - dimethicone- isoeicosane-disteardimonium hectorite - betaine -centella asiatica extract- polygonum cuspidatum root extract - scutellaria baicalensis root extract - camellia sinensis leaf extract - glycyrrhiza glabra (licorice) root extract - chamomilla recutita (matricaria) flower extract - portulaca oleracea extract - rosmarinus officinalis (rosemary) leaf extract - hydrogenated starch hydrolysate - ethylhexylglycerin - tocopheryl acetate - magnesium sulfate - silica - glycosyl trehalose - aluminum hydroxide - palmitic acid - stearic acid - butylene glycol - phenoxyethanol - vinyl dimethicone/methicone silsesquioxane crosspolymer - acrylates/dimethicone copolymer - dimethicone/vinyl dimethicone crosspolymer -methicone - CI 77492/iron oxides - CI 77499/iron oxides - CI 77491/iron oxides